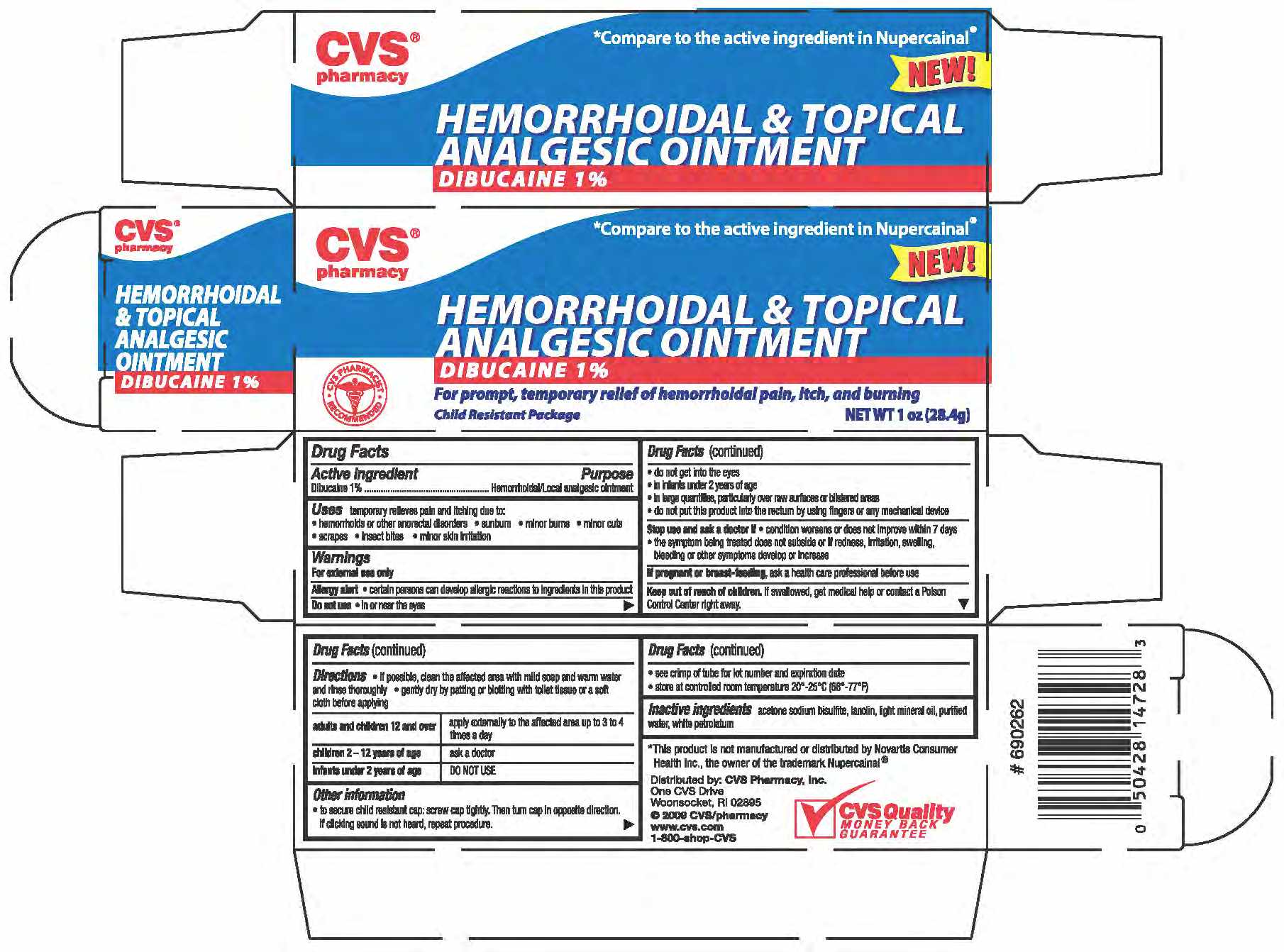 DRUG LABEL: DIBUCAINE
NDC: 59779-398 | Form: CREAM
Manufacturer: CVS Pharmacy
Category: otc | Type: HUMAN OTC DRUG LABEL
Date: 20100716

ACTIVE INGREDIENTS: DIBUCAINE 10 mg/1 g
INACTIVE INGREDIENTS: LANOLIN; ACETONE SODIUM BISULFITE; PETROLATUM; WATER; MINERAL OIL

drug facts

Active ingredients Purpose
Dibucaine 1%...............................................Hemorrhoidal/Local analgesic ointment

Active ingredients Purpose
Dibucaine 1%...............................................Hemorrhoidal/Local analgesic ointment
Uses temporarily relieves pain and itching due to:
- hemorrhoids or other anorectal disorders - sunburn - minor burns - minor cuts
- scrapes - insect bites - minor skin irritation

Keep out of reach of children. If swallowed, get medical help or contact
a Poison Control Center right away.

INDICATIONS AND USAGE

Uses temporarily relieves pain and itching due to:
- hemorrhoids or other anorectal disorders - sunburn - minor burns - minor cuts
- scrapes - insect bites - minor skin irritation
Other information
- to secure child resistant cap; screw cap tightly. Then turn cap in opposite direction.
If clicking sound is not heard, repeat procedure.
- see crimp of tube for lot number and expiration date
-store at controlled room temperature 20 degrees to 25 degrees c (68 degrees to 77 degrees F)

Warnings
For external use only.
Allergy alert - certain persons san develop allergic reactions to ingredients in this product
Do not use
- in or near the eyes
- do not get into the eyes
- in infants under 2 years of age
- in large quantities, particularly over raw surfaces or blistered areas
- do not put this product into rectum by using fingers or any mechanical device
Stop use and ask a doctor if
- condition worsens, or does not improve within 7 days
- the symptom being treated does not subside or if redness, irritation, swelling, bleeding or other symptoms develop or increase
If pregnant or breast feeding, as a health care professional before use
Keep out of the reach of children. If swallowed, get medical help or contact a Poison Control Center right away

Directions
- if possible clean the affected area with mild soap and warm water and rinse thoroughly
- gently dry by patting or blotting with toilet tissue or a soft cloth before applying
Adults and children 12 and over - apply externally to the affected area up to 3 to 4 times a day.
Children under 2 - 12 years of age - ask a doctor
Infants under 2 years of age - DO NOT USE

Inactive Ingredients
acetone sodium bisulfite, lanolin, light mineral oil, purified water, white petrolatum